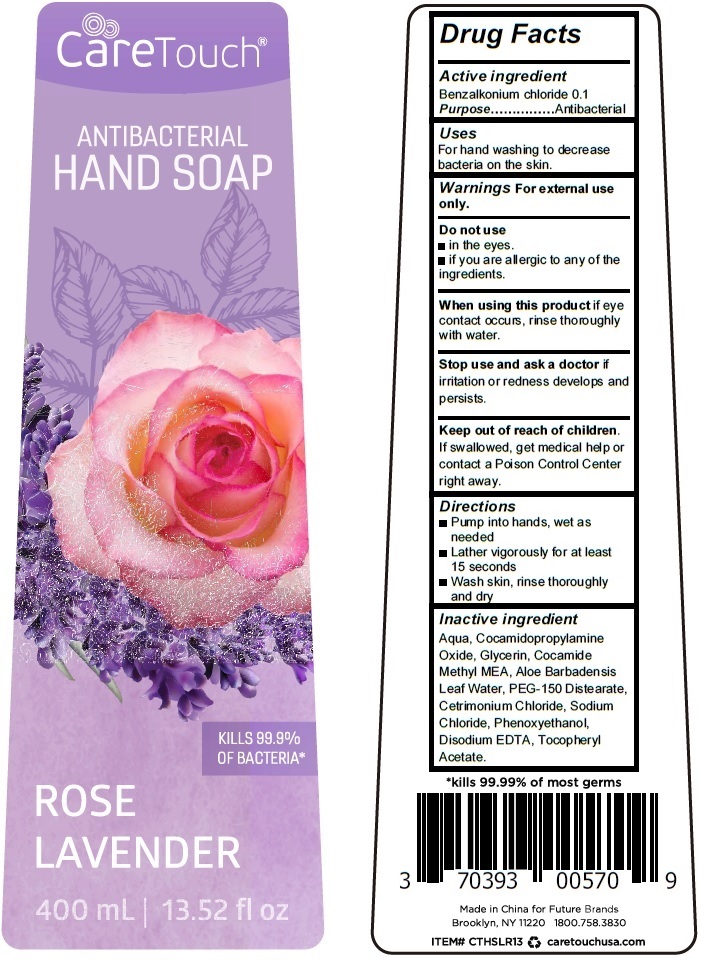 DRUG LABEL: Care Touch Antibacterial HandSoap Rose Lavender
NDC: 70393-052 | Form: LIQUID
Manufacturer: Future Diagnostics Llc
Category: otc | Type: HUMAN OTC DRUG LABEL
Date: 20200831

ACTIVE INGREDIENTS: BENZALKONIUM CHLORIDE 0.1 g/100 mL
INACTIVE INGREDIENTS: WATER; COCAMIDOPROPYLAMINE OXIDE; GLYCERIN; COCOYL METHYL MONOETHANOLAMINE; ALOE VERA LEAF; PEG-150 DISTEARATE; CETRIMONIUM CHLORIDE; SODIUM CHLORIDE; PHENOXYETHANOL; EDETATE DISODIUM ANHYDROUS; .ALPHA.-TOCOPHEROL ACETATE

CareTouch ANTIBACTERIAL HAND SOAP ROSE LAVENDER

Active ingredient

Benzalkonium chloride 0.1

Purpose................................Antibacterial

Uses

For hand washing to decrease bacteria on the skin.

Uses

For hand washing to decrease bacteria on the skin.

Warnings For external use only.

Do not use
• in the eyes.
• if you are allergic to any of the ingredients.

When using this product if eye contact occurs, rinse thoroughly with water.

Stop use and ask a doctor if irritation or redness develops and persists.

Keep out of reach of children.

If swallowed, get medical help or contact a Poison Control Center right away.

Directions

• Pump into hands, wet as needed

• Lather vigorously for at least 15 seconds

• Wash skin, rinse thoroughly and dry

Inactive ingredient

Aqua, Cocamidopropylamine Oxide, Glycerin, Cocamide Methyl MEA, Aloe Barbadensis Leaf Water, PEG-150 Distearate,

Cetrimonium Chloride, Sodium Chloride, Phenoxyethanol, Disodium EDTA, Tocopheryl Acetate.

KILLS 99.99% OF BACTERIA

*kills 99.99% of most germs

Made in China for Future Brands

Brooklyn, NY 11220 1800.758.3830

caretouchusa.com